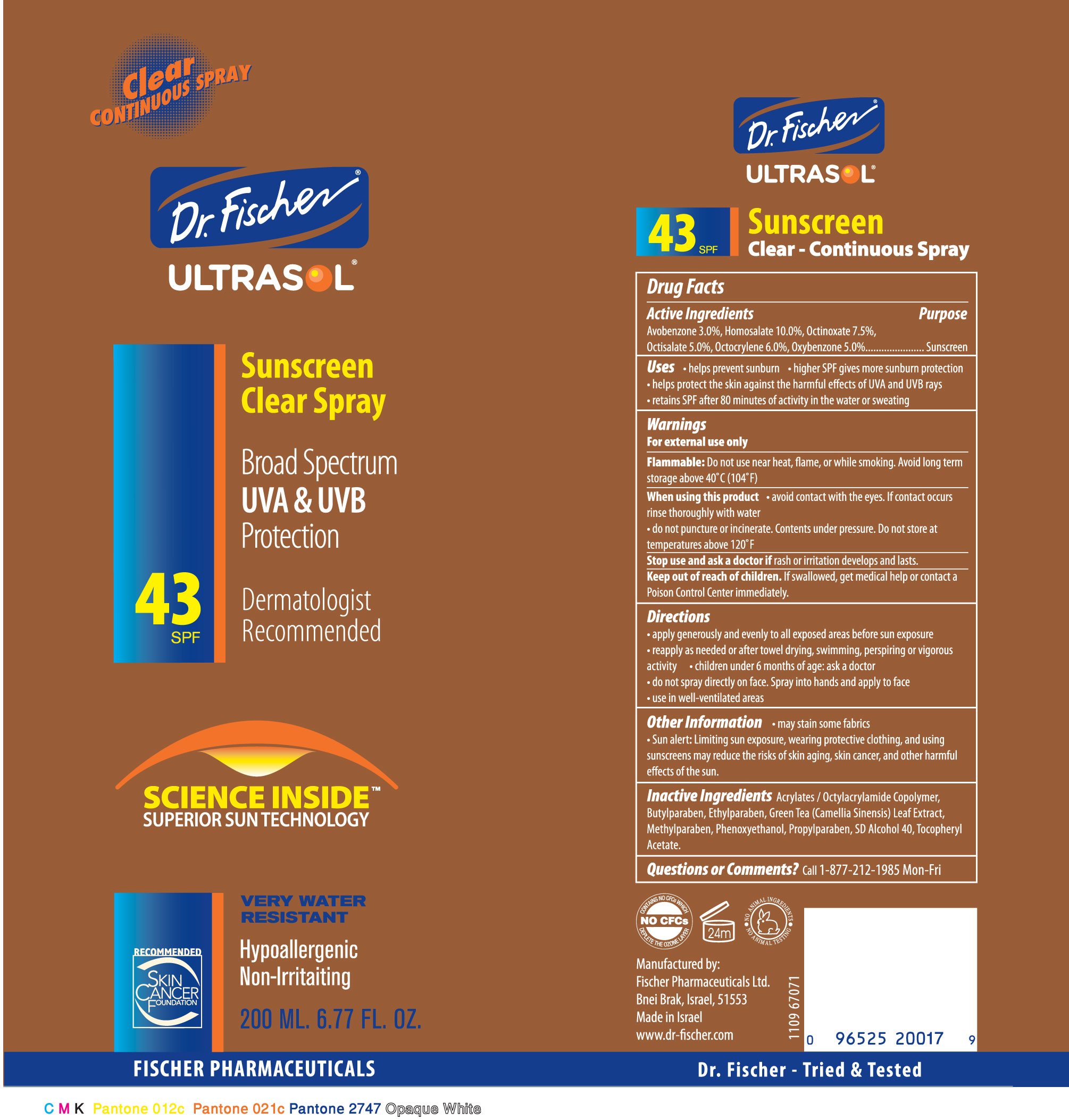 DRUG LABEL: UltrasolSunscreen
NDC: 59886-346 | Form: AEROSOL, SPRAY
Manufacturer: Fischer Pharmaceuticals Ltd
Category: otc | Type: HUMAN OTC DRUG LABEL
Date: 20100323

ACTIVE INGREDIENTS: Avobenzone 3 g/100 g; Homosalate 10 g/100 g; Octinoxate 7.5 g/100 g; Octisalate 5 g/100 g; Octocrylene 6 g/100 g; Oxybenzone 5 g/100 g
INACTIVE INGREDIENTS: Butylparaben; Ethylparaben; Methylparaben; Phenoxyethanol; Propylparaben; Alcohol; ALPHA-TOCOPHEROL ACETATE

Dr. Fischer ULTRASOL Clear CONTINUOUS SPRAY SPF43

Drug Facts

Active Ingredients Purpose
Avobenzone 3.0%, Homosalate 10.0%, Octinoxate 7.5%,
Octisalate 5.0%, Octocrylene 6.0%, Oxybenzone 5.0%...................... Sunscreen

Uses

• helps prevent sunburn • higher SPF gives more sunburn protection
• helps protect the skin against the harmful effects of UVA and UVB rays
• retains SPF after 80 minutes of activity in the water or sweating

Warnings

For external use only

Flammable:

Do not use near heat, flame, or while smoking. Avoid long term
storage above 40˚C (104˚F)

When using this product

• avoid contact with the eyes. If contact occurs
rinse thoroughly with water
• do not puncture or incinerate. Contents under pressure. Do not store at
temperatures above 120˚F

Stop use and ask a doctor if

rash or irritation develops and lasts.

Keep out of reach of children.

If swallowed, get medical help or contact a
Poison Control Center immediately.

Directions

• apply generously and evenly to all exposed areas before sun exposure
• reapply as needed or after towel drying, swimming, perspiring or vigorous
activity • children under 6 months of age: ask a doctor
• do not spray directly on face. Spray into hands and apply to face
• use in well-ventilated areas

Other Information

• may stain some fabrics
• Sun alert: Limiting sun exposure, wearing protective clothing, and using
sunscreens may reduce the risks of skin aging, skin cancer, and other harmful
effects of the sun.

Inactive Ingredients

Acrylates / Octylacrylamide Copolymer,
Butylparaben, Ethylparaben, Green Tea (Camellia Sinensis) Leaf Extract,
Methylparaben, Phenoxyethanol,
Propylparaben, SD Alcohol 40, Tocopheryl Acetate

PACKAGE LABEL

Dr. Fischer

ULTRASOL

Sunscreen Clear Spray SPF43

Clear CONTINUOUS SPRAY

Broad Spectrum UVA and UVB Protection

Dermatologist Recommended

SCIENCE INSIDETM SUPERIOR SUN TECHNOLOGY

VERY WATER RESISTANT

Hypoallergenic

Non Irritating

RECOMMENDED - SKIN CANCER FOUNDATION

200 ML. 6.77 FL. OZ.

FISCHER PHARMACEUTICALS

NO CFCs

24M

NO ANIMAL INGREDIENTS - NO ANIMAL TESTING

Manufactured by:

Fischer Pharmaceuticals Ltd.

Bnei Brak, Israel, 51553

Made in Israel

www.dr-fischer.com

Dr. Fischer - Tried and Tested